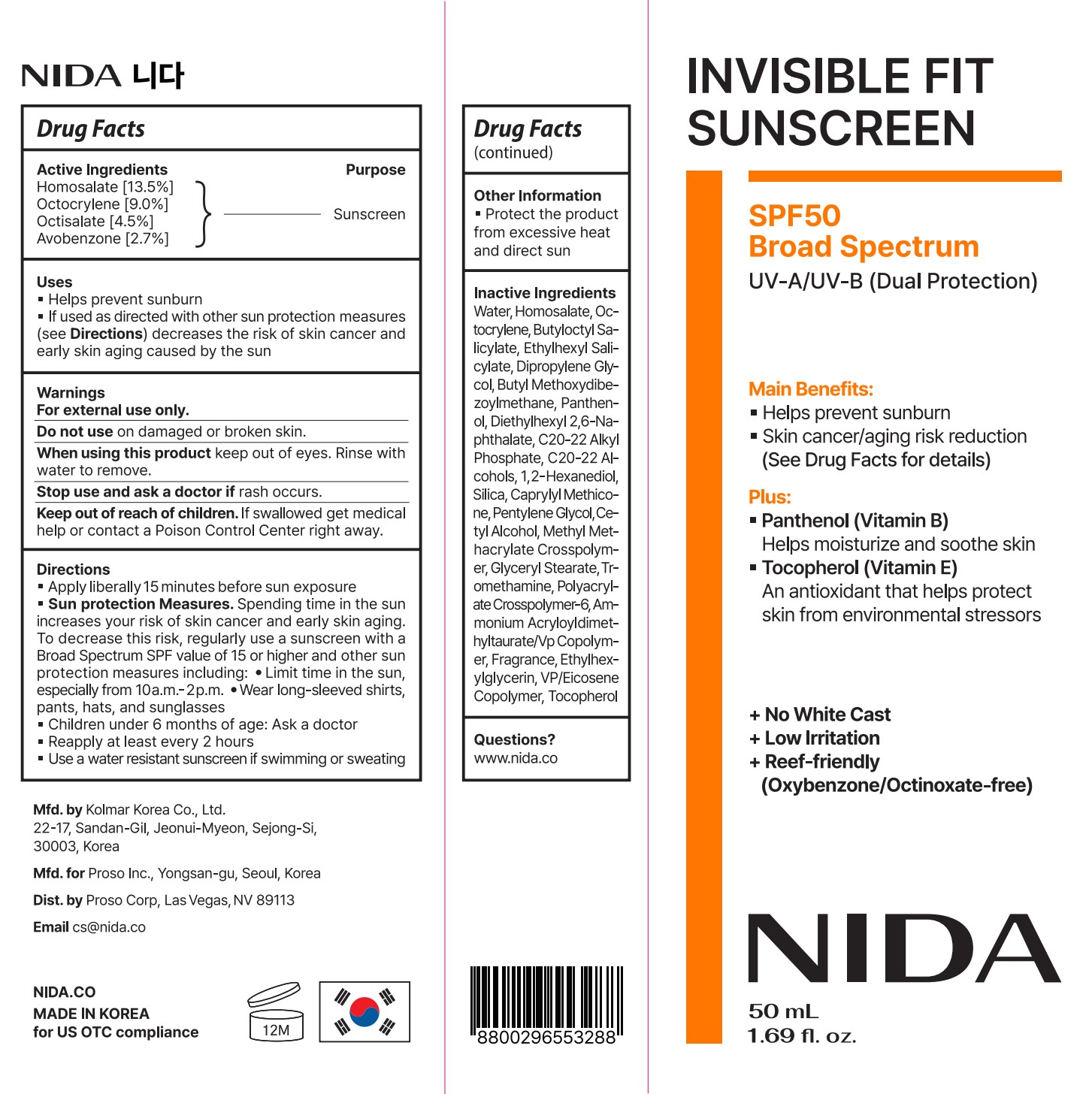 DRUG LABEL: NIDA Invisible Fit Sunscreen
NDC: 87335-001 | Form: CREAM
Manufacturer: Proso Corp
Category: otc | Type: HUMAN OTC DRUG LABEL
Date: 20260108

ACTIVE INGREDIENTS: HOMOSALATE 135 mg/1 g; OCTISALATE 45 mg/1 g; OCTOCRYLENE 90 mg/1 g
INACTIVE INGREDIENTS: ETHYLHEXYLGLYCERIN; TOCOPHEROL; 1,2-HEXANEDIOL; WATER; PANTHENOL; DIETHYLHEXYL 2,6-NAPHTHALATE; GLYCERYL STEARATE; BUTYL METHOXYDIBENZOYLMETHANE; AMMONIUM ACRYLOYLDIMETHYLTAURATE/VP COPOLYMER; C20-22 ALKYL PHOSPHATE; CETYL ALCOHOL; POLYACRYLATE CROSSPOLYMER-6; VINYLPYRROLIDONE/EICOSENE COPOLYMER; DIPROPYLENE GLYCOL; METHYL METHACRYLATE/GLYCOL DIMETHACRYLATE CROSSPOLYMER; TROMETHAMINE; FRAGRANCE FLORAL ORC0902236; BUTYLOCTYL SALICYLATE; C20-22 ALCOHOLS; SILICA; CAPRYLYL METHICONE; PENTYLENE GLYCOL

Directions

Apply liberally 15 minutes before sun exposure

Sun protection Measures. Spending time in the sun increases your risk of skin cancer and early skin aging. To decrease this risk, regularly use a sunscreen with a Broad Spectrum SPF value of 15 or higher and other sun protection measures including: • Limit time in the sun, especially from 10a.m.– 2p.m. • Wear long-sleeved shirts, pants, hats, and sunglasses

Children under 6 months of age: Ask a doctor

Reapply at least every 2 hours

Use a water resistant sunscreen if swimming or sweating

Warnings For external use only.

Do not use on damaged or broken skin.

When using this product keep out of eyes. Rinse with water to remove.

Stop use and ask a doctor if rash occurs.

Keep out of reach of children. If swallowed get medical help or contact a Poison Control Center right away.

Uses

Helps prevent sunburn

If used as directed with other sun protection measures (see Directions) decreases the risk of skin cancer and early skin aging caused by the sun

Keep out of reach of children. If swallowed get medical help or contact a Poison Control Center right away.

Purpose Sunscreen

Active Ingredients

Homosalate [13.5%]

Octocrylene [9.0%]

Octisalate [4.5%]

Avobenzone [2.7%]

Inactive Ingredients

Water, Homosalate, Octocrylene, Butyloctyl Salicylate, Ethylhexyl Salicylate, Dipropylene Glycol, Butyl Methoxydibenzoylmethane, Panthenol, Diethylhexyl 2,6-Naphthalate, C20-22 Alkyl Phosphate, C20-22 Alcohols, 1,2-Hexanediol, Silica, Caprylyl Methicone, Pentylene Glycol, Cetyl Alcohol, Methyl Methacrylate Crosspolymer, Glyceryl Stearate, Tromethamine, Polyacrylate Crosspolymer-6, Ammonium Acryloyldimethyltaurate/Vp Copolymer, Fragrance, Ethylhexylglycerin, VP/Eicosene Copolymer, Tocopherol